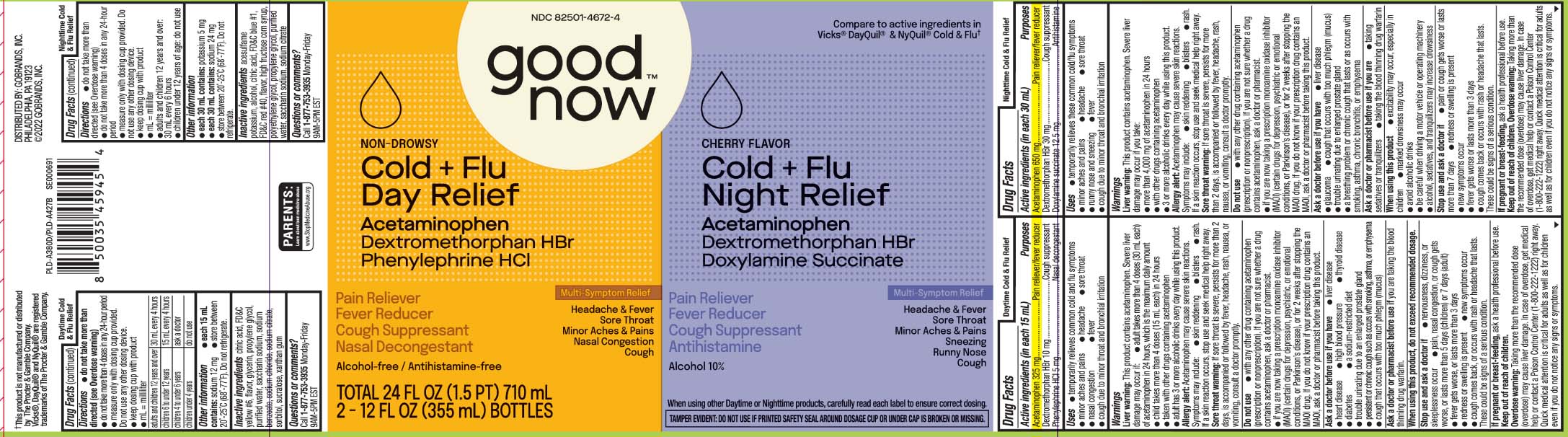 DRUG LABEL: Daytime Nighttime Cold and Flu
NDC: 82501-4672 | Form: KIT | Route: ORAL
Manufacturer: Gobrands, Inc. (Goodnow)
Category: otc | Type: HUMAN OTC DRUG LABEL
Date: 20241015

ACTIVE INGREDIENTS: ACETAMINOPHEN 325 mg/15 mL; DEXTROMETHORPHAN HYDROBROMIDE 10 mg/15 mL; PHENYLEPHRINE HYDROCHLORIDE 5 mg/15 mL; ACETAMINOPHEN 650 mg/30 mL; DEXTROMETHORPHAN HYDROBROMIDE 30 mg/30 mL; DOXYLAMINE SUCCINATE 12.5 mg/30 mL
INACTIVE INGREDIENTS: ANHYDROUS CITRIC ACID; FD&C YELLOW NO. 6; PROPYLENE GLYCOL; WATER; TRISODIUM CITRATE DIHYDRATE; GLYCERIN; SACCHARIN SODIUM; SODIUM BENZOATE; SODIUM CHLORIDE; SORBITOL; SUCRALOSE; XANTHAN GUM; ACESULFAME POTASSIUM; ANHYDROUS CITRIC ACID; ALCOHOL; FD&C BLUE NO. 1; FD&C RED NO. 40; HIGH FRUCTOSE CORN SYRUP; PROPYLENE GLYCOL; WATER; POLYETHYLENE GLYCOL, UNSPECIFIED; TRISODIUM CITRATE DIHYDRATE; SACCHARIN SODIUM

Drug Facts

Active ingredients (in each 15 mL) DAYTIME

Acetaminophen 325 mg

Dextromethorphan HBr 10 mg

Phenylephrine HCl 5 mg

Active ingredients for (in each 30 mL) NIGHTTIME

Acetaminophen 650 mg

Dextromethorphan HBr 30 mg

Doxylamine Succinate 12.5 mg

Purposes for Day Time

Pain reliever/fever reducer

Cough suppressant

Nasal decongestant

Purpose for Night Time

Pain reliever/fever reducer

Cough suppressant

Antihistamine

Uses

DAYTIME

- temporarily relieves common cold and flu symptoms
  - minor aches and pains
  - headache
  - sore throat
  - nasal congestion
  - fever
  - cough due to minor throat and bronchial irritation

NIGHTTIME

- temporarily relieves these common cold/flu symptoms`
  - minor aches and pains
  - headache
  - sore throat
  - runny nose and sneezing
  - fever
  - cough due to minor throat and bronchial irritation

Warnings

DAYTIME

Liver warning: This product contains acetaminophen. Severe liver damage may occur if:

- adult takes more than 4 doses (30 mL each) of acetaminophen in 24 hours, which is the maximum daily amount
- child takes more than 4 doses (15 mL each) in 24 hours
- taken with other drugs containing acetaminophen
- adult has 3 or more alcoholic drinks every day while using this product

Allergy alert: Acetaminophen may cause severe skin reactions. Symptoms may include:

- skin reddening
- blisters
- rash.

If a skin reaction occurs, stop use and seek medical help right away.

Sore throat warning: If sore throat is severe, persists for more than 2 days, is accompanied or followed by fever, headache, rash, nausea, or vomiting, consult a doctor promptly.

NIGHTTIME

Liver warning: This product contains acetaminophen. Severe liver damage may occur if you take:

- more than 4,000 mg of acetaminophen in 24 hours
- with other drugs containing acetaminophen
- 3 or more alcoholic drinks every day while using this product

Allergy alert: Acetaminophen may cause severe skin reactions. Symptoms may include:

- skin reddening
- blisters
- rash.

if a skin reaction occurs, stop use and seek medical help right away.

Sore throat warning: If sore throat is severe, persists for more than 2 days, is accompanied or followed by fever, headache, rash, nausea, or vomiting, consult a doctor promptly.

Do not use

DAYTIME NIGHTTIME

- with any other drug containing acetaminophen (prescription or nonprescription). If you are not sure whether a drug contains acetaminophen, ask a doctor or pharmacist
- If you are taking a prescription monoamine oxidase inhibitor (MAOI) (certain drugs for depression, psychiatric or emotional conditions, or Parkinson's disease), or for 2 weeks after stopping the MAOI drug. If you do not know if your child's prescription drug contains an MAOI, ask a doctor or pharmacist before giving this product.

Ask a doctor before use if you have

DAYTIME

- liver disease
- heart disease
- high blood pressure
- thyroid disease
- diabetes
- a sodium-restricted diet
- trouble urinating due to an enlarged prostate gland
- persistent or chronic cough such as occurs with smoking, asthma, or emphysema
- cough that occurs with too much phlegm (mucus)

NIGHTTIME

- liver disease
- glaucoma
- cough that occurs with too much phlegm (mucus)
- trouble urinating due to an enlarged prostate gland
- a breathing problem or chronic cough that lasts or as occurs with smoking, asthma, chronic bronchitis, or emphysema

Ask a doctor or pharmacist before use if you are

DAYTIME

taking the blood thinning drug warfarin.

NIGHTTIME

- taking sedatives or tranquilizers
- taking the blood thinning drug warfarin

When using this product

DAYTIME

do not exceed recommended dosage.

NIGHTTIME

- excitability may occur, especially in children
- marked drowsiness may occur
- avoid alcoholic drinks
- be careful when driving a motor vehicle or operating machinery
- alcohol, sedatives and tranquilizers may increase drowsiness

Stop use and ask a doctor if

DAYTIME

- nervousness, dizziness or sleeplessness occur
- pain, nasal congestion, or cough gets worse, or lasts more than 5 days(children) or 7 days (adult)
- fever gets worse, or lasts more than 3 days
- redness or swelling is present
- new symptoms occur
- cough comes back, or occurs with rash or headache that lasts.

These could be signs of a serious condition.

NIGHTTIME

- pain or cough gets worse or lasts more than 7 days
- fever gets worse or lasts more than 3 days
- redness or swelling is present
- new symptoms occur
- cough comes back, or occurs with rash, or headache that lasts.

These could be signs of a serious condition.

If pregnant or breast-feeding,

ask a health professional before use.

Keep out of reach of children.

DAYTIME NIGHTTIME

Taking more than the recommended dose (overdose) may cause liver damage. In case of overdose, get medical help or contact a Poison Control Center(1-800-222-1222) right away. Quick medical attention is critical for adults as well as for children even if you do not notice any signs or symptoms.

Directions

DAYTIME

- do not take more than directed (see Overdose warning)
- do not take more than 4 doses in any 24-hour period
- measure only with dosing cup provided. Do not use any other dosing device.
- keep dosing cup with product
- mL= milliliter

adults and children 12 years and over | 30 mL every 4 hours
children 6 to under 12 years | 15 mL every 4 hours
children 4 to under 6 years | ask a doctor
children under 4 years | do not use

NIGHTTIME

- do not take more than directed (see Overdose warning)
- Do not take more than 4 doses in any 24-hours period
- measure only with dosing cup provided. Do not use any other dosing device.
- mL= milliliter
- keep dosing cup with product
- adults and children 12 years and over: 30 mL every 6 hours
- children under 12 years of age: do not use

Other information

DAYTIME

- each 15 mL contains: sodium 12 mg
- store between 20º-25ºC (68º-77º). Do not refrigerate

NIGHTTIME

- each 30 mL contains: potassium 5 mg
- each 30 mL contains sodium 24 mg
- store between 20º-25ºC (68º-77ºF). Do not refrigerate

Inactive ingredients

Day Time

citric acid, FD&C yellow #6, flavor, glycerin, propylene glycol, purified water, saccharin sodium, sodium benzoate, sodium chloride,sodium citrate, sorbitol, sucralose, xantham gum

Night Time

acesulfame potassium, alcohol, anhydrous citric acid, FD&C blue #1, FD&C red #40, flavor, high fructose corn syrup, polyethylene glycol, propylene glycol, purified water, saccharin sodium trisodium citrate dihydrate

Questions or comments?

Call 1-877-753-3935 Monday-Friday 9AM-5PM EST

Principal Display Panel

Compare to active ingredients in Vicks® DayQuil® & NyQuil® Cold & Flu†

DAYTIME

NON-DROWSY

Cold + Flu

Day Relief

Acetaminophen

Dextromethorphan HBr

Phenylephrine HCl

Pain Reliever

Fever Reducer

Cough Suppressant

Nasal Decongestant

Alcohol-free / Antihistamine-free

Multi-Symptom Relief

Headaches & Fever

Sore Throat

Minor Aches & Pains

Nasal Congestion

Cough

NIGHTTIME

CHERRY FLAVOR

Cold + Flu

Night Relief

Acetaminophen

Dextromethorphan HBr

Doxylamine Succinate

Pain Reliever

FeverReducer

Cough Suppressant

Antihistamine

Alcohol 10%

Multi-Symptom Relief

Headache & Fever

Sore Throat

Minor Aches & Pains

Sneezing

Running Nose

Cough

FL OZ (mL)

When using other Daytime or Nighttime products, carefully read each label to ensure correct dosing.

†This product is not manufactured or distributed by The Procter & Gamble Company. Vicks®, DayQuil® and NyQuil® are registered trademarks of The Procter & Gamble Company.

TAMPER EVIDENT: DO NOT USE IF PRINTED SAFETY SEAL AROUND DOSAGE CUP OR UNDER CAP IS BROKEN OR MISSING.

DISTRIBUTED BY: GOBRANDS, INC.

PHILADELPHIA,PA 19123

Product Label

GOOD NOW Cold + Flu Day Relief Cold + Flu Night Relief Cherry Flavor